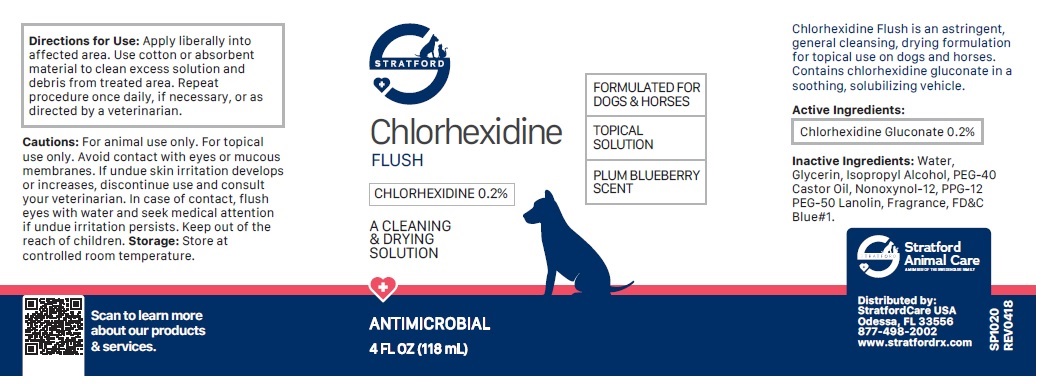 DRUG LABEL: Chlorhexidine FLUSH
NDC: 86069-105 | Form: SOLUTION
Manufacturer: Stratford Care Usa, Inc.
Category: animal | Type: OTC ANIMAL DRUG LABEL
Date: 20221121

ACTIVE INGREDIENTS: CHLORHEXIDINE GLUCONATE 0.2 g/100 mL
INACTIVE INGREDIENTS: WATER; GLYCERIN; ISOPROPYL ALCOHOL; POLYETHYLENE GLYCOL 2000; HYDROGENATED CASTOR OIL; NONOXYNOL-12; PPG-12-PEG-50 LANOLIN; FD&C BLUE NO. 1

Chlorhexidine FLUSH

Active Ingredients:

Chlorhexidine Gluconate 0.2%

PURPOSE

Antimicrobial

INDICATIONS AND USAGE

Chlorhexidine Flush is an astringent, general cleansing, drying formulation for topical use on dogs and horses. Contains chlorhexidine gluconate in a soothing, solubilizing vehicle.

INACTIVE INGREDIENT

Inactive Ingredients: Water, Glycerin, Isopropyl Alcohol, PEG-40 Castor Oil, Nonoxynol-12, PPG-12 PEG-50 Lanolin, Fragrance, FD&C Blue#1.

DOSAGE AND ADMINISTRATION

Directions For Use: Apply liberally into affected area. Use cotton or absorbent material to clean excess solution and debris from treated area. Repeat procedure once daily, if necessary, or as directed by a veterinarian.

PRECAUTIONS

Cautions: For animal use only. For topical use only. Avoid contact with eyes or mucous membranes. If undue skin irritation develops or increases, discontinue use and consult your veterinarian. In case of contact, flush eyes with water and seek medical attention if undue irritation persists. Keep out of the reach of children.

Storage: Store at controlled room temperature.

A CLEANING & DRYING SOLUTION

ANTIMICROBIAL

FORMULATED FOR DOGS & HORSES

TOPICAL SOLUTION

PLUM BLUBERRY SCENT

Stratford Animal Care
A MEMBER OF THE SWEDENCARE FAMILY

Distributed by:
StratfordCare USA
Odessa, FL 33556
877-498-2002
www.stratfordrx.com